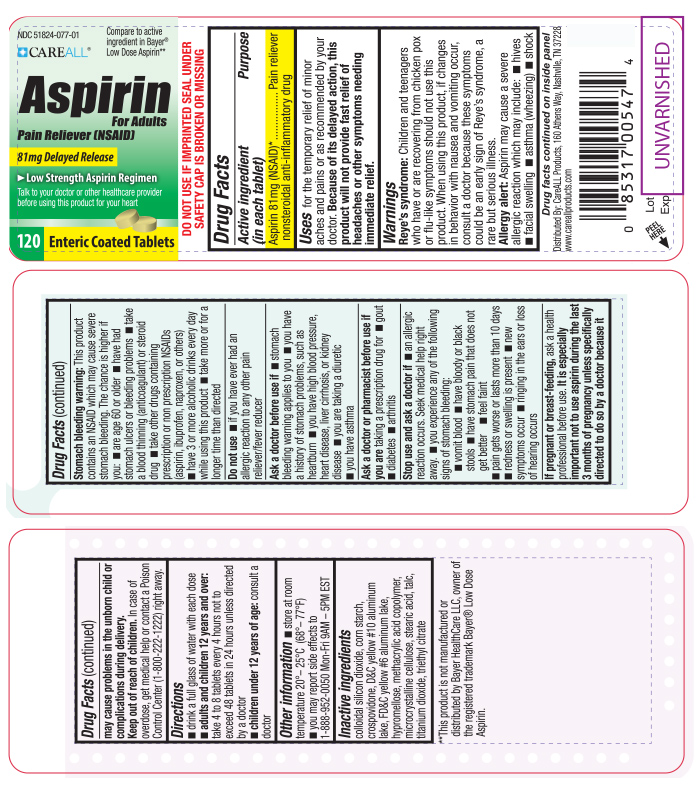 DRUG LABEL: CAREALL Aspirin
NDC: 51824-077 | Form: TABLET, COATED
Manufacturer: New World Imports, Inc
Category: otc | Type: HUMAN OTC DRUG LABEL
Date: 20251201

ACTIVE INGREDIENTS: ASPIRIN 81 mg/1 1
INACTIVE INGREDIENTS: SILICON DIOXIDE; D&C YELLOW NO. 10 ALUMINUM LAKE; METHACRYLIC ACID - METHYL METHACRYLATE COPOLYMER (1:1); CELLULOSE, MICROCRYSTALLINE; TITANIUM DIOXIDE; TRIETHYL CITRATE; TALC; STARCH, CORN; CROSPOVIDONE; FD&C YELLOW NO. 6; HYPROMELLOSES; STEARIC ACID

DRUG FACTS

Active Ingredient

Aspirin 81mg (NSAID*)

*nonsteroidal anti-inflammatory drug

Purpose

Pain Reliever

Keep out of reach of Children. In case of overdose, get medical help or contact a Poison Control Center (1-800-222-1222) right away.

Uses

For the temporary relief of minor aches and pain or as recommended by your doctor. Because of its delayed action, this product will not provide fast relief of headaches or other symptoms needing immediate relief.

Warnings

Reye's Syndrome:Children and teenagers who have or are recovering from chicken pox or flu-like symptoms should not use this product. When using this product, if changes in behavior with nausea and vomiting occur, consult a doctor because these symptoms could be an early sign of Reye's syndrome, a rare but serious illness.

Allergy alert:Aspirin may cause a severe allergic reaction which may included

- hives
- facial swelling
- asthma (wheezing)
- shock

Stomach Bleeding Warning: this product containers an NSAID, which may cause severe stomach bleeding. The chance is higher if you:

- Are age 60 or older
- Have had stomach ulcers or bleeding problems
- Take a blood thinning (anticoagulant) or steroid drug
- Take other drugs containing prescription or nonprescription NSAIDs (aspirin, ibuprofen, naproxen, or others)
- Have 3 or more alcoholic drinks every day while using this product
- Take more or for a longer time than directed

Do not use if you are allergic to aspirin or any other pain reliever / fever reducer

Ask a doctor before use if:

- Stomach bleeding warning applies to you
- You have a history of stomach problems, such as heartburn
- You have high blood pressure, heart disease, liver cirrhosis, or kidney disease
- You have asthma
- You have taken a diuretic

Ask a doctor or pharmacist before use ifyou are taking a prescription drug for:

- diabetes
- gout
- arthritis

Stop use and ask a doctor if:

- An allergic reaction occurs. Seek medical help right away
- You experience any of the following signs of stomach bleeding: feel faint, vomit blood, have bloody or black stools, have stomach pain that does not get better
- Redness or swelling is present
- Ringing in the ears or loss of hearing occurs
- Pain gets worse or lasts more than 10 days

If pregnant or breast-feeding, ask a health professional before use. It is especially important not to use aspirin during the last 3 months of pregnancy unless specifically directed to do so by a doctor because it may cause problems in the unborn child or complications during delivery.

Directions

Drink a full glass of water with each dose

Adults and children 12 years and over:take 4 to 8 tablets every 4 hours not to exceed 48 tablets in 24 hours unless directed by a doctor.

Children under 12 years of age:consult a doctor

Inactive Ingredients

colloidal silicon dioxide, corn starch, crospovidone, D C yellow 10 aluminum lake, FD C yellow 6 aluminum lake, hypromellose, methacrylic acid copolymer, microcrystalline cellulose, stearic acid, talc, titanium dioxide, triethyl ceitrate